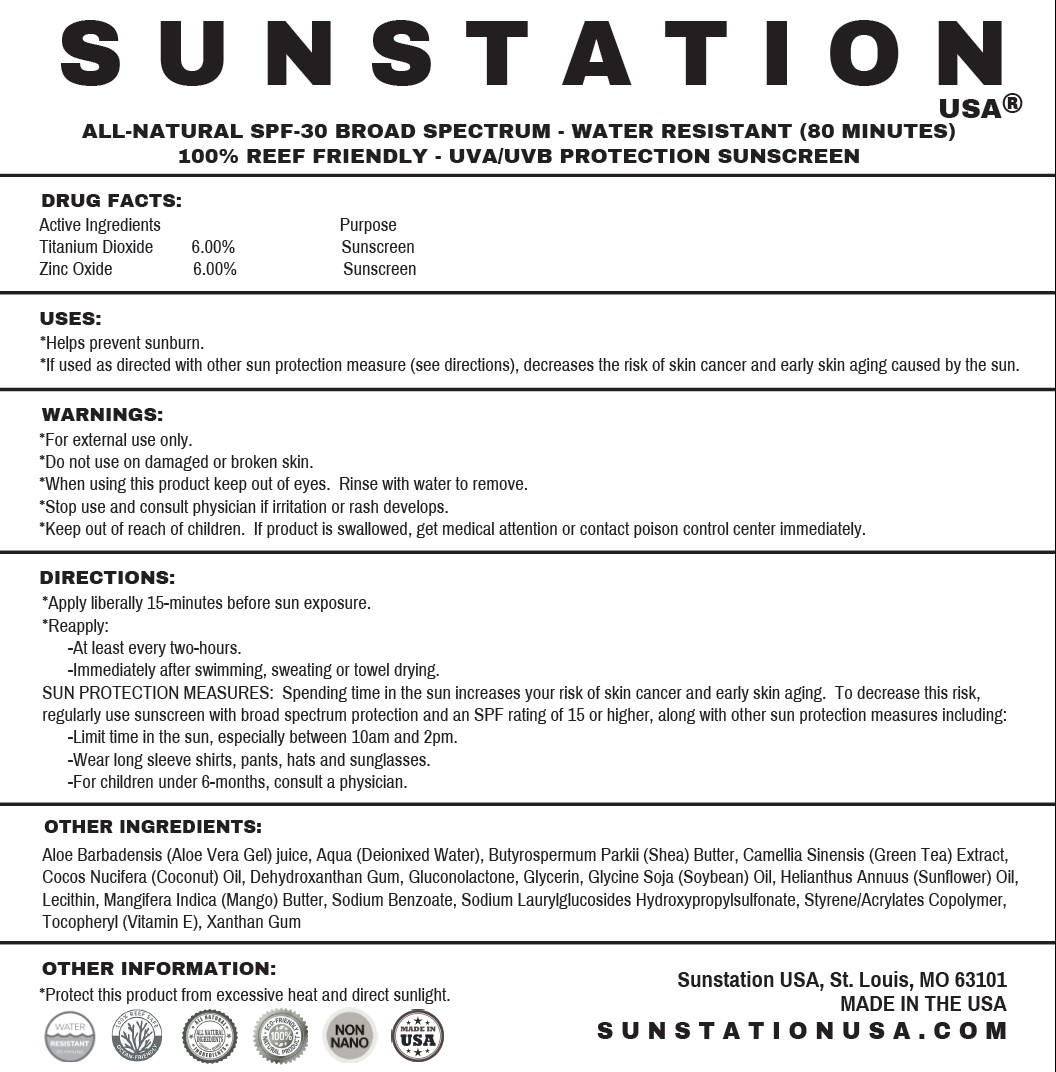 DRUG LABEL: Sunstation All-Natural SPF 30 Sunscreen
NDC: 71272-811 | Form: LOTION
Manufacturer: Sunstation USA, LLC
Category: otc | Type: HUMAN OTC DRUG LABEL
Date: 20231111

ACTIVE INGREDIENTS: TITANIUM DIOXIDE 60 mg/1 g; ZINC OXIDE 60 mg/1 g
INACTIVE INGREDIENTS: GLUCONOLACTONE; GLYCERIN; SOYBEAN OIL; HELIANTHUS ANNUUS FLOWERING TOP; MANGO; SODIUM BENZOATE; .ALPHA.-TOCOPHEROL; XANTHAN GUM; ALOE VERA LEAF; WATER; SHEA BUTTER; GREEN TEA LEAF; COCONUT OIL; DEHYDROXANTHAN GUM

Sunstation All-Natural SPF-30 Sunscreen

Active Ingredients

Titanium Dioxide 6.00%

Zinc Oxide 6.00%

Purpose

Sunscreen

Uses:

- Helps prevent sunburn.
- If used as directed with other sun protection measure (see directions), decreases the risk of skin cancer and early skin aging caused by the sun.

Warnings

- For external use only.

Do not use

on damaged or broken skin.

When using this product

keep out of eyes. Rinse with water to remove.

Stop use and consult physician if

irritation or rash develops.

Keep out of reach of children.

If product is swallowed, get medical attention or contact poison control center immediately.

Directions:

- Apply liberally 15-minutes before sun exposure

- At least every two-hours.
- Immediately after swimming, sweating or towel drying.

- Limit time in the sun, especially between 10am and 2pm.
- Wear long sleeve shirts, pants, hats and sunglasses.
- For children under 6-months, consult a physician.

Reapply:

SUN PROTECTION MEASURES: Spending time in the sun increases your risk of skin cancer and early skin aging. To decrease this risk, regularly use sunscreen with broad spectrum protection and an SPF rating of 15 or higher, along with other sun protection measures including:

OTHER INGREDIENTS:

Aloe Barbadensis (Aloe Vera Gel) juice, Aqua (Deionixed Water), Butyrospermum Parkii (Shea) Butter, Camellia Sinensis (Green Tea) Extract, Cocos Nucifera (Coconut) Oil, Dehydroxanthan Gum, Gluconolactone, Glycerin, Glycine Soja (Soybean) Oil, Helianthus Annuus (Sunflower) Oil, Lecithin, Mangifera Indica (Mango) Butter, Sodium Benzoate, Sodium Laurylglucosides Hydroxypropylsulfonate, Styrene/Acrylates Copolymer, Tocopheryl (Vitamin E), Xanthan Gum

OTHER INFORMATIONS:

- Protect this product from excessive heat and direct sunlight.